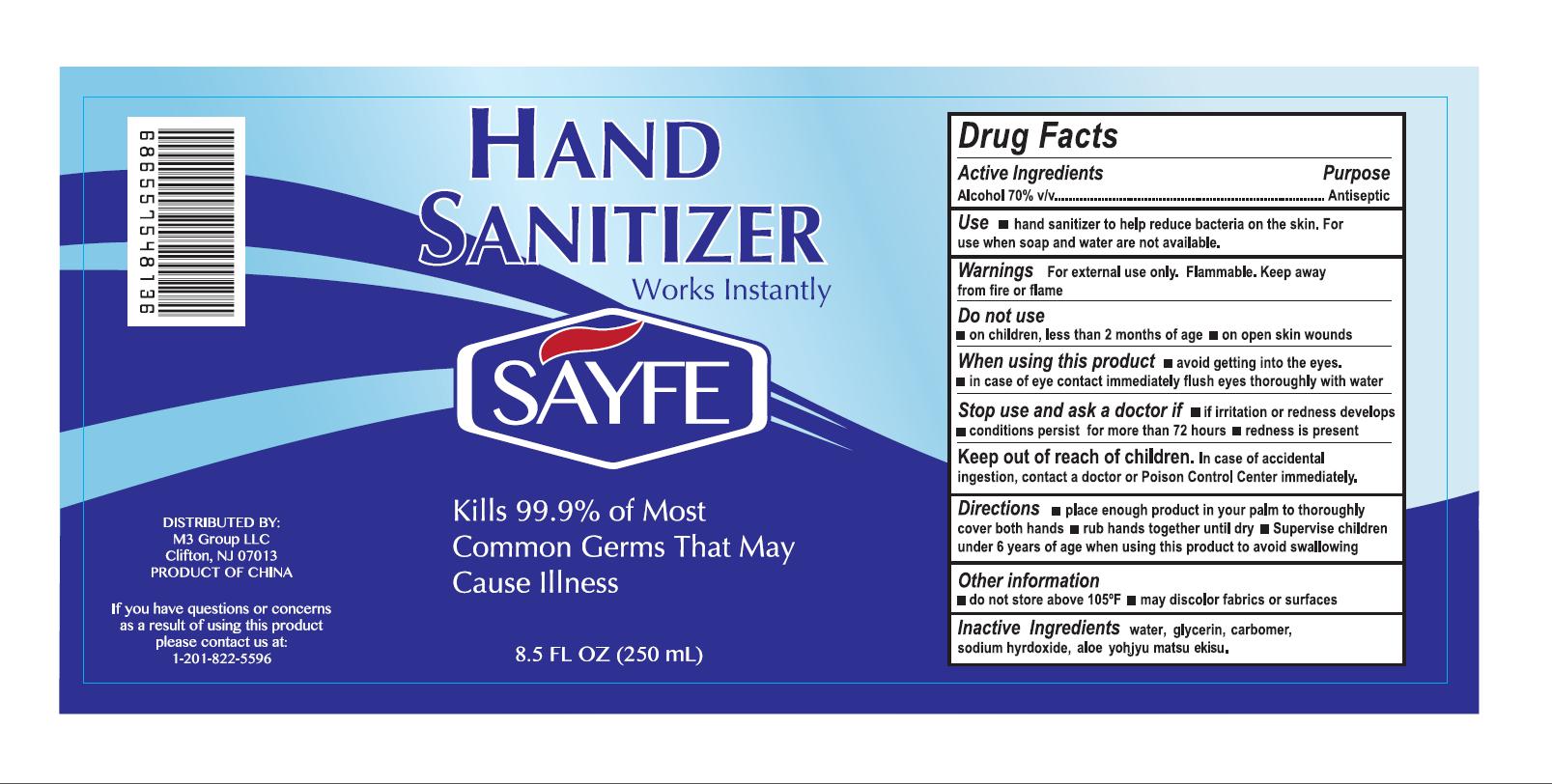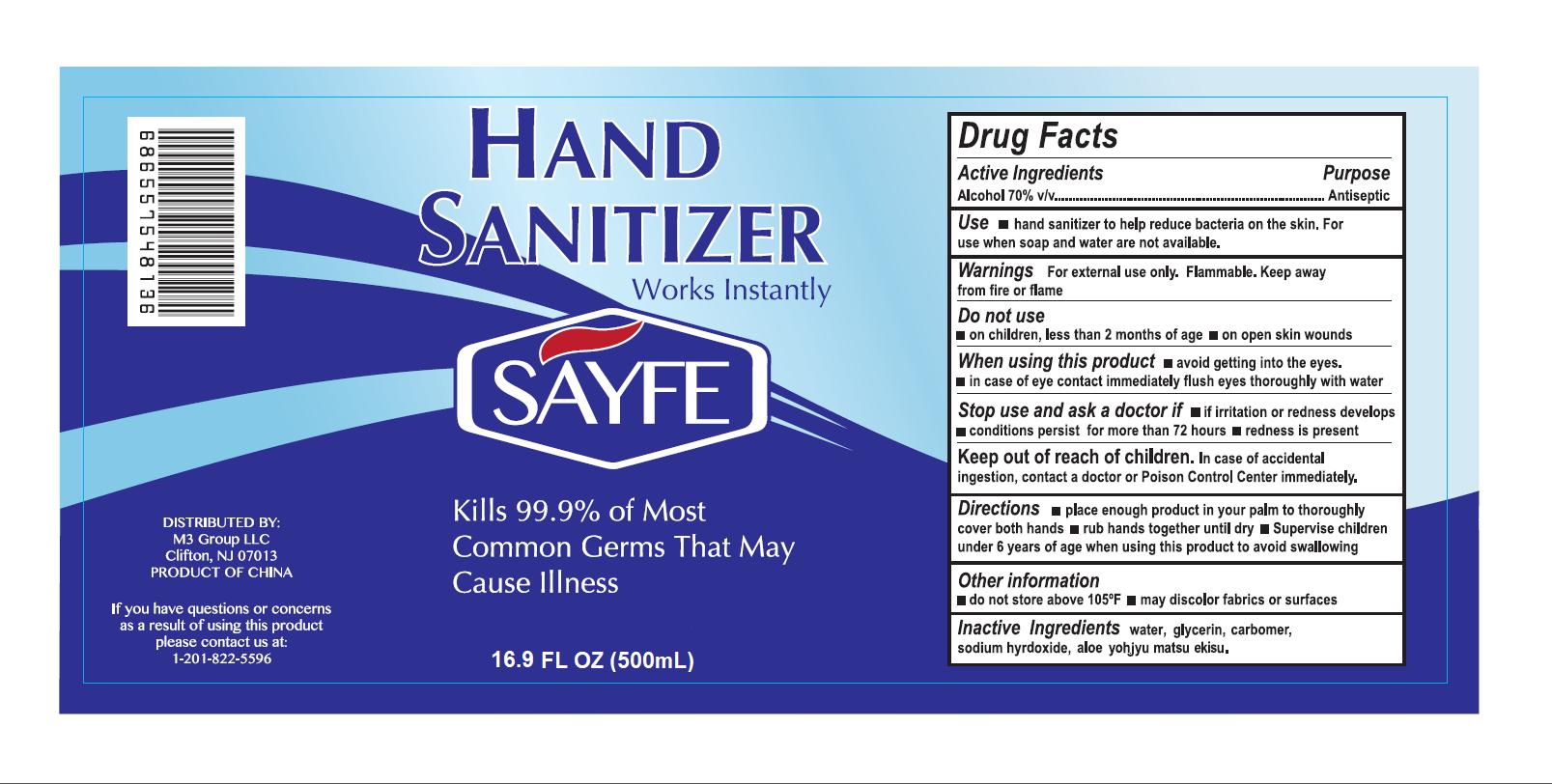 DRUG LABEL: Hand Sanitizer
NDC: 75675-005 | Form: LIQUID
Manufacturer: GUANGZHOU CANYON BIOTECHNOLOGY CO.,LTD
Category: otc | Type: HUMAN OTC DRUG LABEL
Date: 20200418

ACTIVE INGREDIENTS: ALCOHOL 70 mL/100 mL
INACTIVE INGREDIENTS: SODIUM HYDROXIDE 0.05 g/100 mL; GLYCERIN 3 g/100 mL; CARBOMER 934 0.65 g/100 mL; WATER; ALOE 0.1 g/100 mL

Active Ingredient(s)

Alcohol 70% v/v. Purpose: Antiseptic

Purpose

Antiseptic, Hand Sanitizer

Use

Hand Sanitizer to help reduce bacteria that potentially can cause disease. For use when soap and water are not available.

Warnings

For external use only. Flammable. Keep away from heat or flame

Do not use

- in children less than 2 months of age
- on open skin wounds

When using this product a avoid getting into the eyes. in case of eye contact immediately flush eyes thoroughly with water.

Stop use and ask a doctor if irritation or redness develops.conditions persist for more than 72 hours m redness is present.

Keep out of reach of children.In case of accidental ingestion, contact a doctor or Poison Control Center immediately.

Directions

- Place enough product on hands to cover all surfaces. Rub hands together until dry.
- Supervise children under 6 years of age when using this product to avoid swallowing.

Other information

- do not store above 105"F
- may discolor fabrics or surfaces

Inactive ingredients

water, glycerin, carbomer sodium hyrdoxide, aloe yohjyu matsu ekisu.